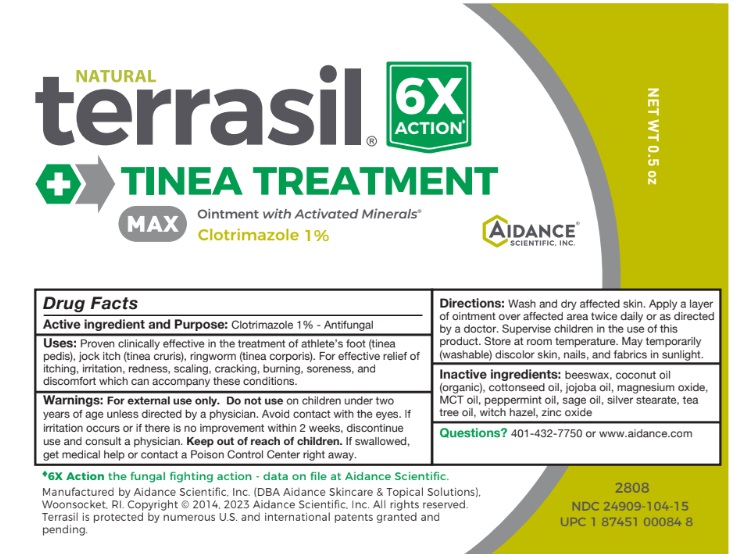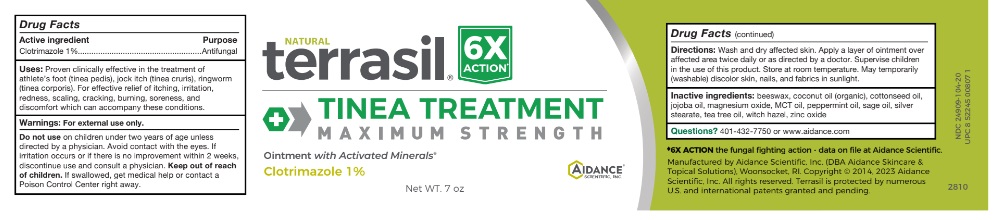 DRUG LABEL: Terrasil Tinea Treatment
NDC: 24909-104 | Form: OINTMENT
Manufacturer: Aidance Scientific, Inc., DBA Aidance Skincare & Topical Solutions
Category: otc | Type: HUMAN OTC DRUG LABEL
Date: 20250711

ACTIVE INGREDIENTS: CLOTRIMAZOLE 1 g/100 g
INACTIVE INGREDIENTS: YELLOW WAX; COCONUT OIL; COTTONSEED OIL; JOJOBA OIL; MAGNESIUM OXIDE; PALM OIL; PEPPERMINT OIL; SAGE OIL; SILVER STEARATE; TEA TREE OIL; WITCH HAZEL; ZINC OXIDE

24909-104 terrasil Tinea Treatment Max

Active ingredient

Clotrimazole 1%

Purpose

Antifungal

Uses

Proven clinically effective in the treatment of athlete’s foot (tinea pedis), jock itch (tinea cruris), ringworm (tinea corporis). For effective relief of itching, irritation, redness, scaling, cracking, burning, soreness, and discomfort which can accompany these conditions.

Warnings

For external use only. Do not useon children under two years of age unless directed by a physician. Avoid contact with the eyes. If irritation occurs or if there is no improvement within 4 weeks, discontinue use and consult a physician.

Keep out of reach of children.

Directions

Wash and dry affected skin. Apply a thin layer of ointment over the affected area twice daily (morning and night) or as directed by a doctor. Supervise children in the use of this product. Store at room temperature. May stain fabrics.

Inactive ingredients

beeswax, coconut oil (organic), cottonseed oil, jojoba oil, magnesium oxide, MCT oil, peppermint oil, sage oil, silver stearate, tea tree oil, witch hazel, zinc oxide